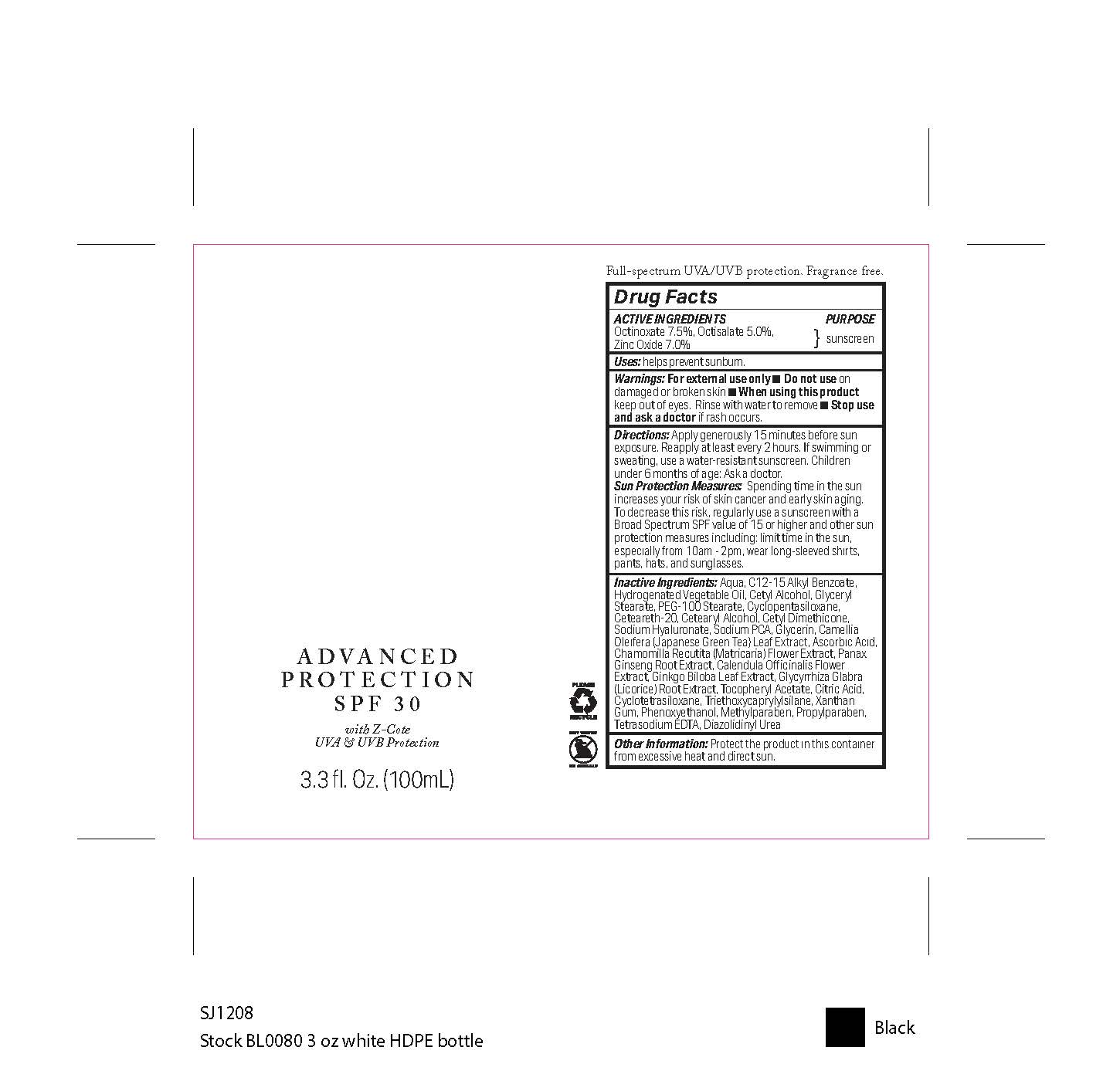 DRUG LABEL: ADVANCED PROTECTION SUNSCREEN SPF-30
NDC: 70712-103 | Form: LOTION
Manufacturer: BOTANICAL SCIENCE, INC.
Category: otc | Type: HUMAN OTC DRUG LABEL
Date: 20250304

ACTIVE INGREDIENTS: OCTINOXATE 7.5 g/100 mL; OCTISALATE 5 g/100 mL; ZINC OXIDE 7 g/100 mL
INACTIVE INGREDIENTS: METHYLPARABEN; DIAZOLIDINYL UREA; SODIUM HYALURONATE; .ALPHA.-TOCOPHEROL ACETATE; PROPYLPARABEN; SODIUM PCA; PHENOXYETHANOL; TETRASODIUM EDTA; CAMELLIA OLEIFERA LEAF; ALKYL (C12-15) BENZOATE; CETYL ALCOHOL; WATER; HYDROGENATED PALM OIL; GLYCERYL MONOSTEARATE; GLYCERIN; CALENDULA OFFICINALIS FLOWER; MATRICARIA CHAMOMILLA FLOWERING TOP; PEG-100 STEARATE; XANTHAN GUM; TRIETHOXYCAPRYLYLSILANE; CYCLOPENTASILOXANE; CETEARETH-20; CYCLOMETHICONE 4; ASCORBIC ACID; CETEARYL ALCOHOL; GINKGO BILOBA LEAF; ASIAN GINSENG; GLYCYRRHIZA GLABRA (LICORICE) ROOT; CITRIC ACID

BOTANICAL SCIENCE - ADVANCED PROTECTION SUNSCREEN SPF-30 (70712-103)

ACTIVE INGREDIENTS

ZINC OXIDE 7.0%

OCTINOXATE 7.5%

OCTISALATE 5.0%

PURPOSE

SUNSCREEN

USES

HELPS PREVENT SUNBURN.

WARNINGS

FOR EXTERNAL USE ONLY.

- Do not use on damaged or broken skin.
- When using this product keep out of eyes. Rinse with water to remove.
- Stop use and ask a doctor if rash occurs.

DIRECTIONS

APPLY GENEROUSLY 15 MINUTES BEFORE SUN EXPOSURE. REAPPLY AT LEAST EVERY 2 HOURS. IF SWIMMING OR SWEATING, USE A WATER-RESISTANT SUNSCREEN. CHILDREN UNDER 6 MONTHS OF AGE: ASK A DOCTOR.

SUN PROTECTION MEASURES

SPENDING TIME IN THE SUN INCREASES YOUR RISK OF SKIN CANCER AND EARLY SKIN AGING. TO DECREASE THIS RISK, REGULARLY USE A SUNSCREEN WITH A BROAD SPECTRUM SPF VALUE OF 15 OR HIGHER AND OTHER SUN PROTECTION MEASURES INCLUDING: LIMIT TIME IN THE SUN, ESPECIALLY FROM 10AM - 2PM, WEAR LONG-SLEEVED SHIRTS, PANTS, HATS, AND SUNGLASSES.

Keep out of reach of children.

INACTIVE INGREDIENTS

AQUA, C12-15 ALKYL BENZOATE, HYDROGENATED VEGETABLE OIL, CETYL ALCOHOL, GLYCERYL STEARATE, PEG-100 STEARATE, CYCLOPENTASILOXANE, CETEARETH-20, CETEARYL ALCOHOL, CETYL DIMETHICONE, SODIUM HYALURONATE, SODIUM PCA, GLYCERIN, CAMELLIA OLEIFERA (JAPANESE GREEN TEA) LEAF EXTRACT, ASCORBIC ACID, CHAMOMILLA RECUTITA (MATRICARIA) FLOWER EXTRACT, PANAX GINSENG ROOT EXTRACT, CALENDULA OFFICINALIS FLOWER EXTRACT, GINKGO BILOBA LEAF EXTRACT, GLYCYRRHIZA GLABRA (LICORICE) ROOT EXTRACT, TOCOPHERYL ACETATE, CITRIC ACID, CYCLOTETRASILOXANE, TRIETHOXYCAPRYLYLSILANE, XANTHAN GUM, PHENOXYETHANOL, METHYLPARABEN, PROPYLPARABEN, TETRASODIUM EDTA, DIAZOLIDINYL UREA